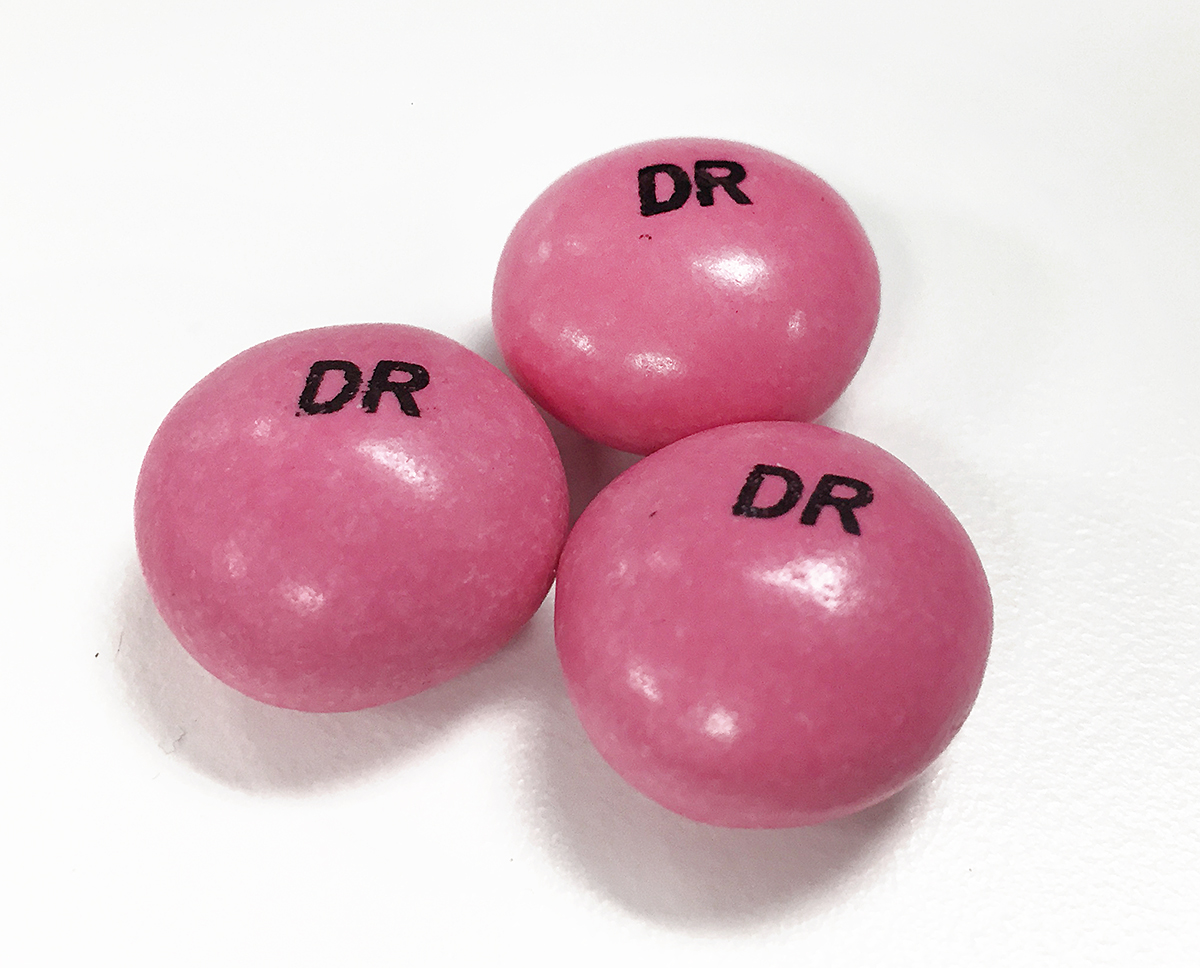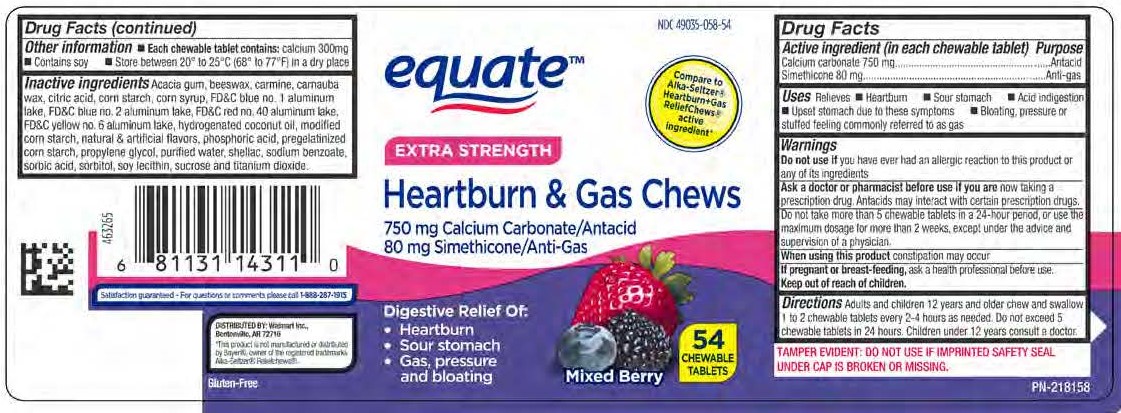 DRUG LABEL: Mixed Berry Antacid and Anti-Gas Chews
NDC: 49035-058 | Form: TABLET, CHEWABLE
Manufacturer: Walmart Stores
Category: otc | Type: HUMAN OTC DRUG LABEL
Date: 20251223

ACTIVE INGREDIENTS: DIMETHICONE 80 mg/1 1; CALCIUM CARBONATE 750 mg/1 1
INACTIVE INGREDIENTS: SUCROSE

Calcium Carbonate 750 mg
Simethicone 80 mg

Active ingredient (in each chewable tablet)

Calcium Carbonate 750 mg

Simethicone 80 mg

Purpose

Antacid

Anti-gas

INDICATIONS AND USAGE

Uses: Relieves

- Heartburn
- Sour stomach
- Acid indigestion
- Upset stomach associated to these symptoms
- Bloating, pressure or stuffed feeling commonly referred to as gas

Warnings

Do not use if you have ever had an allergic reaction to this product or any of its ingredients.

Ask a doctor or pharmacist before use if you are now taking a prescription drug. Antacids may interact with certain prescription drugs.

WHEN USING

Do not take more than 5 chews in a 24-hour period, or use the maximum dosage for more than 2 weeks, except under the advice and supervision of a physician.

When using this product constipation may occur

PREGNANCY OR BREAST FEEDING

If pregnant or breast-feeding, ask a health professional before use.

Keep out of reach of children.

DOSAGE AND ADMINISTRATION

Directions - Adults and children 12 years and older chew and swallow 1 to 2 chews every 2-4 hours as needed. Do not exceed 5 chews in 24-hours. Children under 12 years consult a doctor.

Other information

- Each chewable tablet contains: calcium 300 mg
- Contains soy
- Store between 20° to 25°C (68° to 77°F) in a dry place

INACTIVE INGREDIENT

Inactive ingredients: Acacia gum, beeswax, carmine, carnauba wax, citric acid, corn starch, corn syrup, FD&C blue no. 1 aluminum lake, FD&C blue no. 2 aluminum lake, FD&C red no. 40 aluminum lake, FD&C yellow no. 6 aluminum lake, hydrogenated coconut oil, modified corn starch, natural and artificial flavors, phosphoric acid, pregelatinized corn starch, propylene glycol, purified water, shellac, sodium benzoate, sorbic acid, sorbitol, soy lecithin, sucrose, and titanium dioxide.

Questions? Call 1-888-287-1915